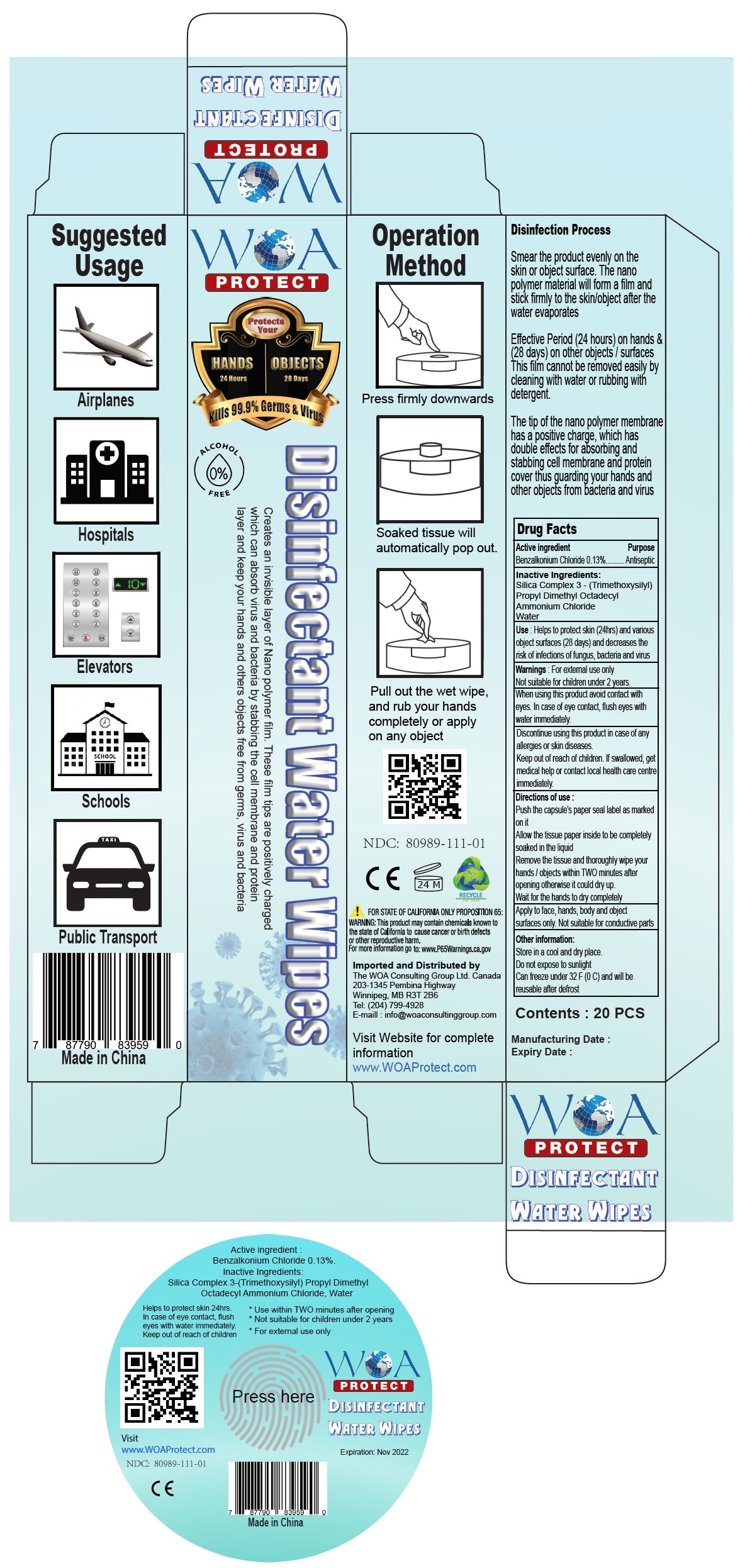 DRUG LABEL: WOA PROTECT
NDC: 80989-111 | Form: CLOTH
Manufacturer: The Woa Consulting Group Ltd
Category: otc | Type: HUMAN OTC DRUG LABEL
Date: 20201125

ACTIVE INGREDIENTS: BENZALKONIUM CHLORIDE 0.13 g/100 mL
INACTIVE INGREDIENTS: DIMETHYLOCTADECYL(3-(TRIMETHOXYSILYL)PROPYL)AMMONIUM CHLORIDE; WATER

WOA PROTECT Disinfectant Water Wipes

Active ingredient

Benzalkonium Chloride 0.13%

Purpose

Antiseptic

Inactive Ingredients:

Silica Complex 3 - (Trimethoxysilyl) Propyl Dimethyl Octadecyl Ammonium Chloride, Water

Use:

Helps to protect skin (24hrs) and various object surfaces (28 days) and decreases the risk of infections of fungus, bacteria and virus

Warnings:

For external use only

Not suitable for children under 2 years.

When using this product avoid contact with eyes. In case of eye contact, flush eyes with water immediately.

Discontinue using this product in case of any allergies or skin diseases.

Keep out of reach of children. If swallowed, get medical help or contact local health care centre immediately.

Directions of use:

Push the capsule's paper seal label as marked on it

Allow the tissue paper inside to be completely soaked in the liquid

Remove the tissue and thoroughly wipe your hands / objects within TWO minutes after opening otherwise it could dry up.

Wait for the hands to dry completely

Apply to face, hands, body and object surfaces only. Not suitable for conductive parts

Other information:

Store in a cool and dry place.

Do not expose to sunlight

Can freeze under 32 F (0 C) and will be reusable after defrost

Protects Your

HANDS 24 hours

OBJECTS 28 days

Kills 99.9% Germs & Virus

ALCOHOL 0% FREE

Creates an invisible layer of Nano polymer film. These film tips are positively charged which can absorb virus and bacteria by stabbing the cell membrane and protein layer and keep your hands and others objects free from germs, virus and bacteria

Disinfection Process

Smear the product evenly on the skin or object surface. The nano polymer material will form a film and stick firmly to the skin/object after the water evaporates

Effective Period (24 hours) on hands & (28 days) on other objects / surfaces. This film cannot be removed easily by cleaning with water or rubbing with detergent.

The tip of the nano polymer membrane has a positive charge, which has double effects for absorbing and stabbing cell membrane and protein cover thus guarding your hands and other objects from bacteria and virus

Suggested Usage

Airplanes

Hospitals

Elevators

Schools

Public Transport

Operation Method

Press firmly downwards

Soaked tissue will automatically pop out.

Pull out the wet wipe, and rub your hands completely or apply on any object

FOR STATE OF CALIFORNIA ONLY PROPOSITION 65:

WARNING: This product may contain chemicals known to the state of California to cause cancer or birth defects or other reproductive harm.

For more information go to: www.P65Warnings.ca.gov

Imported and Distributed by

The WOA Consulting Group Ltd. Canada

203-1345 Pembina Highway

Winnipeg, MB R3T 2B6

Tel: (204) 799-4928

E-mail : info@woaconsultinggroup.com

Visit Website for complete information

www.WOAProtect.com

Made in China